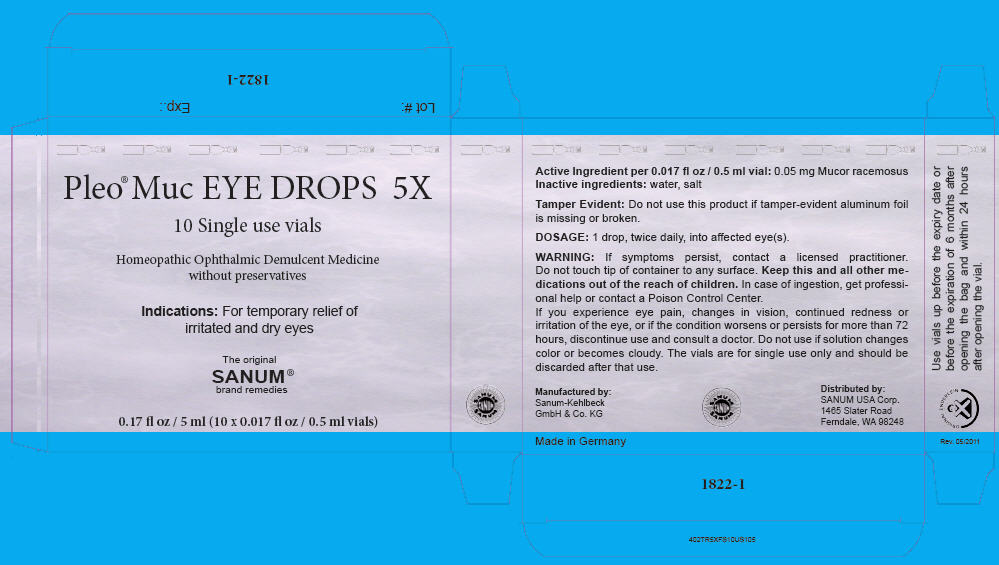 DRUG LABEL: Pleo Muc
NDC: 60681-1822 | Form: LIQUID
Manufacturer: Sanum Kehlbeck GmbH & Co KG
Category: homeopathic | Type: HUMAN OTC DRUG LABEL
Date: 20120208

ACTIVE INGREDIENTS: mucor racemosus 5 [hp_X]/1 mL
INACTIVE INGREDIENTS: water; sodium chloride

Pleo® Muc EYE DROPS 5X

PURPOSE

Homeopathic Ophthalmic Demulcent Medicine without preservatives

Indications

For temporary relief of irritated and dry eyes

Active Ingredient per 0.017 fl oz / 0.5 ml vial

0.05 mg Mucor racemosus

Inactive ingredient

water, salt

Tamper Evident

Do not use this product if tamper-evident aluminum foil is missing or broken.

DOSAGE

1 drop, twice daily, into affected eye(s).

WARNING

ASK DOCTOR

If symptoms persist, contact a licensed practitioner.

WHEN USING

Do not touch tip of container to any surface.

KEEP OUT OF REACH OF CHILDREN

Keep this and all other medications out of the reach of children. In case of ingestion, get professional help or contact a Poison Control Center.

STOP USE

If you experience eye pain, changes in vision, continued redness or irritation of the eye, or if the condition worsens or persists for more than 72 hours, discontinue use and consult a doctor.

Do not use if solution changes color or becomes cloudy. The vials are for single use only and should be discarded after that use.

Distributed by:
SANUM USA Corp.
1465 Slater Road
Ferndale, WA 98248

Manufactured by:
Sanum-Kehlbeck
GmbH & Co. KG

PRINCIPAL DISPLAY PANEL - 5 ml Carton

Pleo® Muc EYE DROPS 5X

10 Single use vials

Homeopathic Ophthalmic Demulcent Medicine
without preservatives

Indications: For temporary relief of
irritated and dry eyes

The original
SANUM®
brand remedies

0.17 fl oz / 5 ml (10 x 0.017 fl oz / 0.5 ml vials)